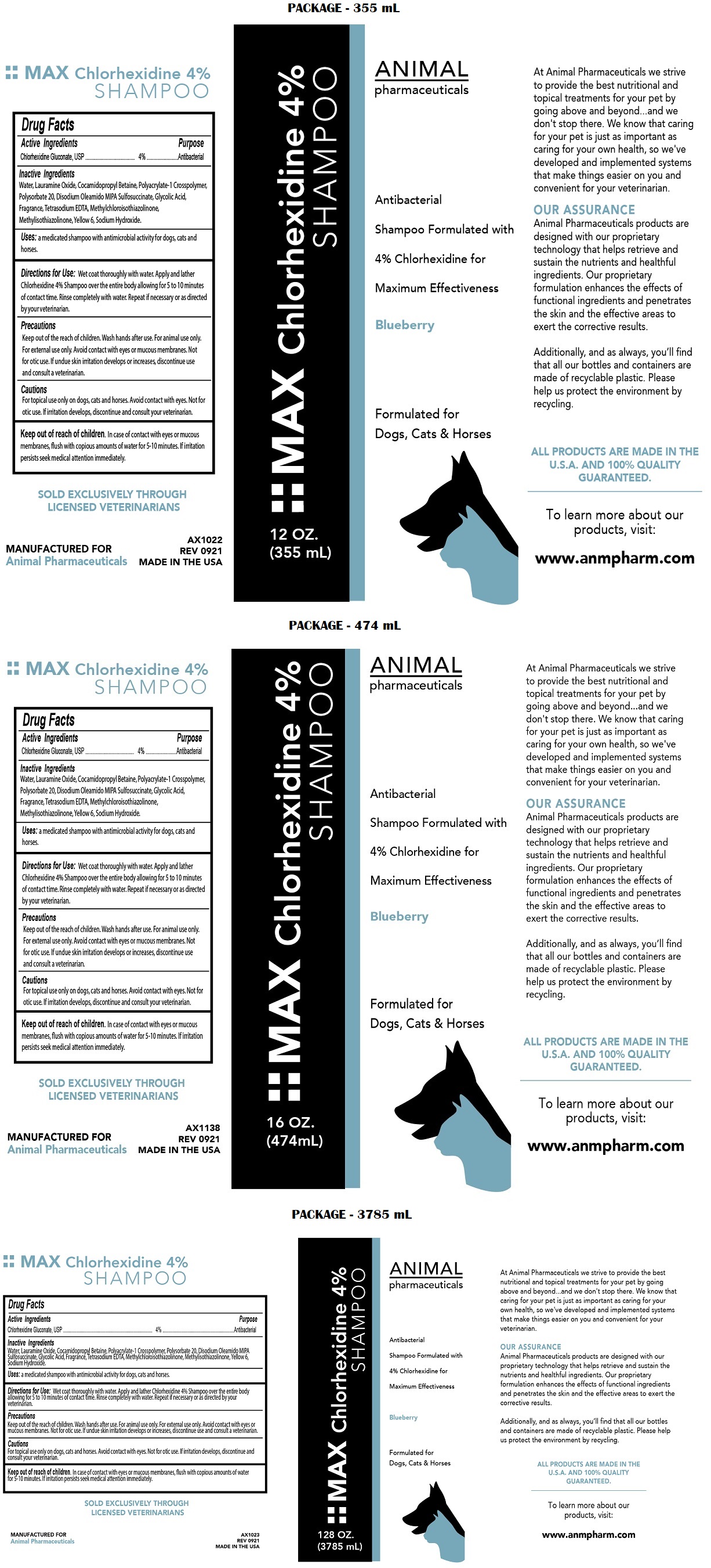 DRUG LABEL: MAX Chlorhexidine 4%
NDC: 68898-123 | Form: SHAMPOO
Manufacturer: Animal Pharmaceuticals
Category: animal | Type: OTC ANIMAL DRUG LABEL
Date: 20221121

ACTIVE INGREDIENTS: CHLORHEXIDINE GLUCONATE 4 g/100 mL
INACTIVE INGREDIENTS: WATER; LAURAMINE OXIDE; COCAMIDOPROPYL BETAINE; POLYSORBATE 20; DISODIUM OLEAMIDO MIPA-SULFOSUCCINATE; GLYCOLIC ACID; EDETATE SODIUM; METHYLCHLOROISOTHIAZOLINONE; METHYLISOTHIAZOLINONE; FD&C YELLOW NO. 6; SODIUM HYDROXIDE

MAX Chlorhexidine 4% SHAMPOO

Active Ingredients

Chlorhexidine Gluconate, USP 4%

Purpose

Antibacterial

Inactive Ingredients

Water, Lauramine Oxide, Cocamidopropyl Betaine, Polyacrylate-1 Crosspolymer, Polysorbate 20, Disodium Oleamido MIPA Sulfosuccinate, Glycolic Acid, Fragrance, Tetrasodium EDTA, Methylchloroisothiazolinone, Methylisothiazolinone, Yellow 6, Sodium Hydroxide

Uses:

a medicated shampoo with antimicrobial activity for dogs, cats, and horses.

Directions for Use:

Wet coat thoroughly with water. Apply and lather Chlorhexidine 4% Shampoo over the entire body allowing for 5 to 10 minutes of contact time. Rinse completely with water. Repeat if necessary or as directed by your veterinarian.

Precautions

Keep out of the reach of children. Wash hands after use. For animal use only. For external use only. Avoid contact with eyes or mucous membranes. Not for otic use. If undue skin irritation develops or increases, discontinue use and consult a veterinarian.

Cautions

For topical use only on dogs, cats and horses. Avoid contact with eyes. Not for otic use. If irritation develops, discontinue and consult your veterinarian.

Keep out of reach of children. In case of contact with eyes or mucous membranes, flush with copious amounts of water for 5-10 minutes. If irritation persists seek medical attention immediately.

Antibacterial Shampoo Formulated with 4% Chlorhexidine for Maximum Effectiveness

Blueberry

Formulated for Dogs, Cats & Horses

At Animal Pharmaceuticals we strive to provide the best nutritional and topical treatments for your pet by going above and beyond....and we don't stop there. We know that caring for your pet is just as important as caring for your own health, so we've developed and implemented systems that make things easier on you and convenient for your veterinarian.

OUR ASSURANCE
Animal Pharmaceuticals products are designed with our proprietary technology that helps retrieve and sustain the nutrients and healthful ingredients. Our proprietary formulation enhances the effects of functional ingredients and penetrates the skin and the effective areas to exert the corrective results.

Additionally, and as always, you'll find that all our bottles and containers are made of recyclable plastic. Please help us protect the environment by recycling.

ALL PRODUCTS ARE MADE IN THE U.S.A. AND 100% QUALITY GUARANTEED.

To learn more about our products, visit:

www.anmpharm.com

SOLD EXCLUSIVELY THROUGH LICENSED VETERINARIANS

MANUFACTURED FOR
Animal Pharmaceuticals

MADE IN THE USA